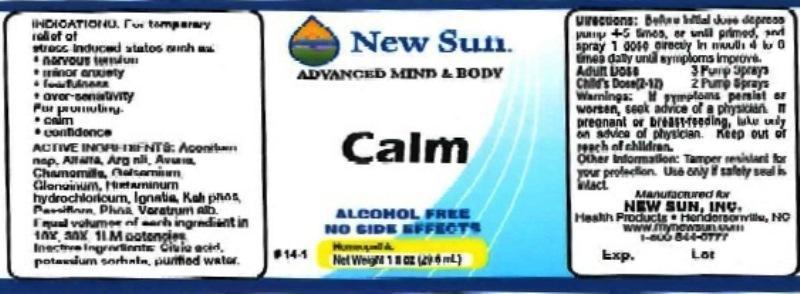 DRUG LABEL: Calm
NDC: 66579-0049 | Form: LIQUID
Manufacturer: New Sun Inc.
Category: homeopathic | Type: HUMAN OTC DRUG LABEL
Date: 20161123

ACTIVE INGREDIENTS: ACONITUM NAPELLUS 10 [hp_X]/29 mL; ALFALFA 10 [hp_X]/29 mL; SILVER NITRATE 10 [hp_X]/29 mL; AVENA SATIVA FLOWERING TOP 10 [hp_X]/29 mL; MATRICARIA RECUTITA 10 [hp_X]/29 mL; GELSEMIUM SEMPERVIRENS ROOT 10 [hp_X]/29 mL; NITROGLYCERIN 10 [hp_X]/29 mL; HISTAMINE DIHYDROCHLORIDE 10 [hp_X]/29 mL; STRYCHNOS IGNATII SEED 10 [hp_X]/29 mL; POTASSIUM PHOSPHATE, DIBASIC 10 [hp_X]/29 mL; PASSIFLORA INCARNATA FLOWERING TOP 10 [hp_X]/29 mL; PHOSPHORUS 10 [hp_X]/29 mL; VERATRUM ALBUM ROOT 10 [hp_X]/29 mL
INACTIVE INGREDIENTS: ANHYDROUS CITRIC ACID; POTASSIUM SORBATE; WATER

Calm

DOSAGE AND ADMINISTRATION

Directions: Before initial dose depress pump 4-5 times or until primed and spray 1 dose directly in mouth 4 to 6 times daily until symptoms improve.

Adult Dose: 3 Pump Sprays

Child's Dose (2-12): 2 Pump Sprays

WARNINGS

Warnings: If symptoms persist or worsen, seek advice of physician. If pregnant or breast-feeding, take only on advice of physician.

Keep out of reach of children.

Other information: Tamper resistant for your protection. Use only if safety seal is intact.

PURPOSE

Indications: For temporary relief of: stress induced states such as: •nervous tension •minor anxieties •fearfulness •over-sensitivity

ACTIVE INGREDIENT

Active Ingredients: Aconitum napellus, Alfalfa, Argentum nitricum, Avena sativa, Chamomilla, Gelsemium sempervirens, Glonoinum, Histaminum hydrochloricum, Ignatia amara, Kali phosphoricum, Passiflora incarnata, Phosphorus, Veratrum album. Equal volumes of each ingredient in 10X, 30X, 1LM potencies.

Inactive Ingredient: Citric acid, potassium sorbate, purified water.

INDICATIONS AND USAGE

Indications: For temporary relief of: stress induced states such as:

- nervous tension
- minor anxiety
- fearfulness
- over-sensitivity

For promoting:

- calm
- confidence